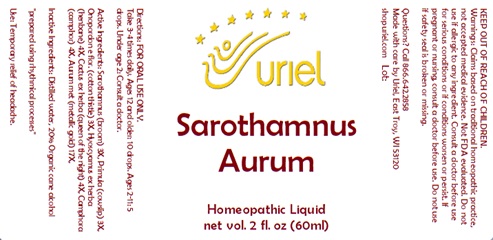 DRUG LABEL: Sarothamnus Aurum
NDC: 48951-8404 | Form: LIQUID
Manufacturer: Uriel Pharmacy, Inc.
Category: homeopathic | Type: HUMAN OTC DRUG LABEL
Date: 20231218

ACTIVE INGREDIENTS: SELENICEREUS GRANDIFLORUS STEM 4 [hp_X]/1 mL; CAMPHOR (NATURAL) 4 [hp_X]/1 mL; GOLD 17 [hp_X]/1 mL; CYTISUS SCOPARIUS FLOWER 3 [hp_X]/1 mL; PRIMULA VERIS FLOWER 3 [hp_X]/1 mL; ONOPORDUM ACANTHIUM FLOWER 3 [hp_X]/1 mL; HYOSCYAMUS NIGER LEAF 4 [hp_X]/1 mL
INACTIVE INGREDIENTS: ALCOHOL; WATER

Sarothamnus Aurum

INDICATIONS AND USAGE

Directions: FOR ORAL USE ONLY.

DOSAGE AND ADMINISTRATION

Take 3-4 times daily. Ages 12 and older: 10 drops. Ages 2-11: 5 drops. Under age 2: Consult a doctor.

ACTIVE INGREDIENT

Active Ingredients: Sarothamnus (broom) 3X, Primula (cowslip) 3X, Onopordon (cotton thistle) 3X, Cactus (queen of the night) 4X, Camphora (camphor) 4X, Hyoscyamus (henbane) 4X, Aurum met (metallic gold) 17X

Inactive Ingredients: Distilled water, 20% Organic cane alcohol

"prepared using rhythmical processes"

PURPOSE

Use: Temporary relief of headache.

KEEP OUT OF REACH OF CHILDREN.

WARNINGS

Warnings: Claims based on traditional homeopathic practice, not accepted medical evidence. Not FDA evaluated. Do not use if allergic to any ingredient. Consult a doctor before use for serious conditions or if conditions worsen or persist. If pregnant or nursing, consult a doctor before use. Do not use if safety seal is broken or missing.

Questions? Call 866.642.2858
Made with care by Uriel, East Troy, WI 53120
shopuriel.com Lot: